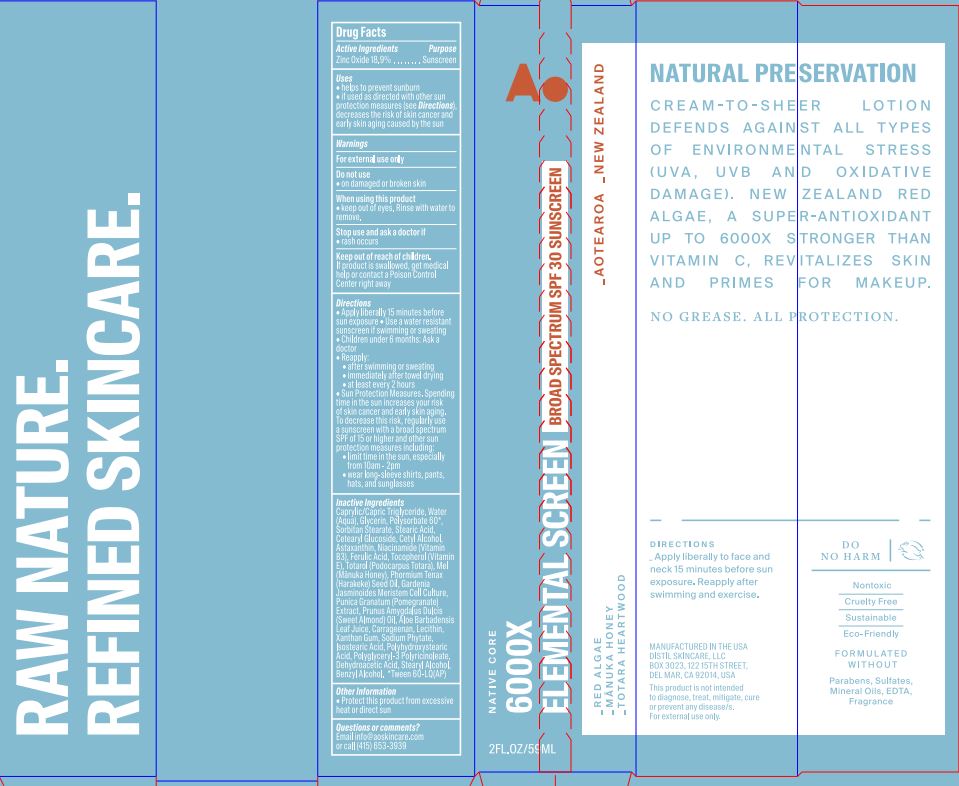 DRUG LABEL: 6000X Elemental Screen BS SPF 30 Sunscreen
NDC: 62742-4241 | Form: CREAM
Manufacturer: Allure Labs
Category: otc | Type: HUMAN OTC DRUG LABEL
Date: 20231212

ACTIVE INGREDIENTS: ZINC OXIDE 18.9 g/100 g
INACTIVE INGREDIENTS: SORBITAN MONOSTEARATE; GARDENIA JASMINOIDES FRUIT; ALMOND OIL; ALOE VERA LEAF; LECITHIN, SOYBEAN; PHYTATE SODIUM; ISOSTEARIC ACID; CETYL ALCOHOL; NIACINAMIDE; TOTAROL; PHORMIUM TENAX SEED OIL; CARRAGEENAN; CETEARYL GLUCOSIDE; GLYCERIN; PUNICA GRANATUM ROOT BARK; BENZYL ALCOHOL; WATER; FERULIC ACID; TOCOPHEROL; HONEY; STEARIC ACID; MEDIUM-CHAIN TRIGLYCERIDES; ASTAXANTHIN; STEARYL ALCOHOL; XANTHAN GUM; POLYSORBATE 60; POLYHYDROXYSTEARIC ACID (2300 MW); POLYGLYCERYL-3 PENTARICINOLEATE; DEHYDROACETIC ACID

Drug Facts

Active Ingredients:

Zinc Oxide 18.9%

Purpose: Sunscreen

INDICATIONS AND USAGE

Uses • helps to prevent sunburn • if used as directed with other sun protection measures (see Directions), decreases the risk of skin cancer and early skin aging caused by the sun.

Warnings For external use only

Do not use • on damaged or broken skin.

When using this product • keep out of eyes. Rinse with water to remove.

Stop use and ask a doctor • rash occurs.

Keep out of reach of children. If product is swallowed, get medical help or contact a Poison Control Center right away.

DOSAGE AND ADMINISTRATION

Directions • Apply liberally 15 minutes before sun exposure • Use a water-resistant sunscreen if swimming or sweating • Children under 6 months: Ask a doctor • Reapply: • after swimming or sweating • immediately after towel drying • at least every 2 hours • Sun Protection Measures. Spending time in the sun increases your risk of skin cancer and early skin aging. To decrease this risk, regularly use a sunscreen with a broad-spectrum SPF of 15 or higher and other sun protection measures including: • limit time in the sun, especially from 10am - 2pm • wear long-sleeve shirts, pants, hats, and sunglasses.

Other information • Protect this product from excessive heat or direct sun.

Inactive Ingredients:

Caprylic/Capric Triglyceride, Water (Aqua), Glycerin, Polysorbate 60*, Sorbitan Stearate, Stearic Acid, Cetearyl Glucoside, Cetyl Alcohol, Astaxanthin, Niacinamide (Vitamin B3), Ferulic Acid, Tocopherol (Vitamin E), Totarol (Podocarpus Totara), Mel (Manuka Honey), Phormium Tenax (Harakeke) Seed Oil, Gardenia Jasminoides Meristem Cell Culture, Punica Granatum (Pomegranate) Extract, Prunus Amygdalus Dulcis (Sweet Almond) Oil, Aloe Barbadensis Leaf Juice, Carrageenan, Lecithin, Xanthan Gum, Sodium Phytate, Isostearic Acid, Polyhydroxystearic Acid, Polyglyceryl-3 Polyricinoleate, Dehydroacetic Acid, Stearyl Alcohol, Benzyl Alcohol. *Tween 60-LQ(AP)